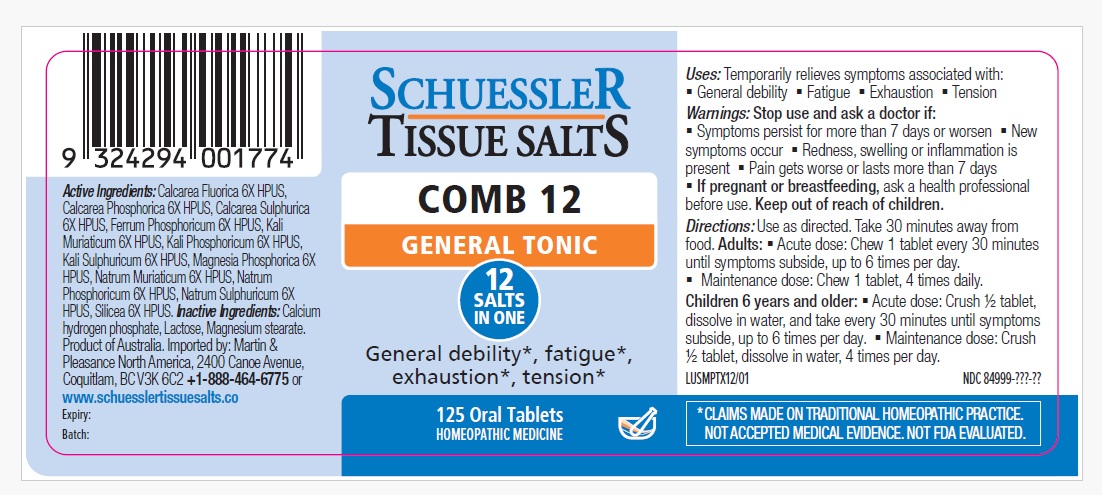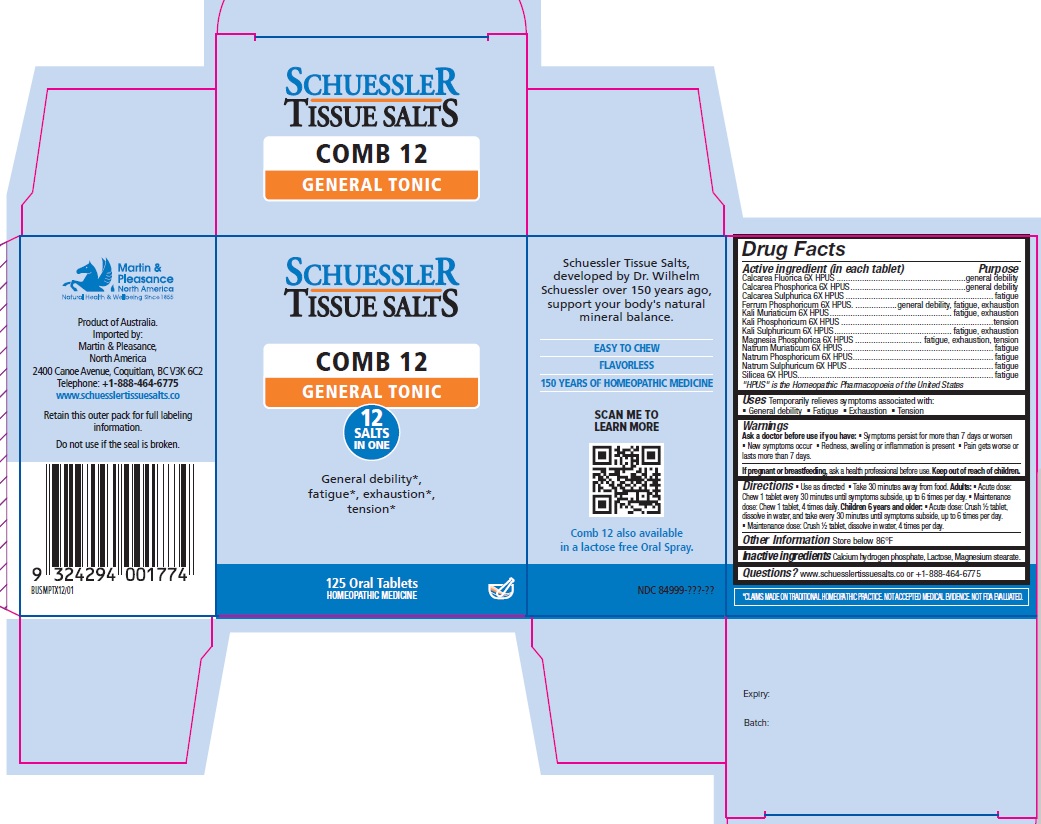 DRUG LABEL: Schuessler Tissue Salts Comb 12 General Tonic
NDC: 84999-029 | Form: TABLET, CHEWABLE
Manufacturer: Martin & Pleasance Pty Ltd
Category: homeopathic | Type: HUMAN OTC DRUG LABEL
Date: 20250909

ACTIVE INGREDIENTS: CALCIUM FLUORIDE 6 [hp_X]/1 1; TRIBASIC CALCIUM PHOSPHATE 6 [hp_X]/1 1; CALCIUM SULFATE DIHYDRATE 6 [hp_X]/1 1; FERROUS PHOSPHATE 6 [hp_X]/1 1; DIBASIC POTASSIUM PHOSPHATE 6 [hp_X]/1 1; POTASSIUM CHLORIDE 6 [hp_X]/1 1; POTASSIUM SULFATE 6 [hp_X]/1 1; MAGNESIUM PHOSPHATE, DIBASIC 6 [hp_X]/1 1; SODIUM CHLORIDE 6 [hp_X]/1 1; SODIUM PHOSPHATE, DIBASIC, ANHYDROUS 6 [hp_X]/1 1; SODIUM SULFATE ANHYDROUS 6 [hp_X]/1 1; SILICON DIOXIDE 6 [hp_X]/1 1
INACTIVE INGREDIENTS: LACTOSE MONOHYDRATE; MAGNESIUM STEARATE; ANHYDROUS DIBASIC CALCIUM PHOSPHATE

Active Ingredients Purpose

Calcarea Fluorica 6X HPUS ........................................................general debility
Calcarea Phosphorica 6X HPUS..................................................general debility
Calcarea Sulphurica 6X HPUS ................................................................ fatigue
Ferrum Phosphoricum 6X HPUS. ..................general debility, fatigue, exhaustion
Kali Muriaticum 6X HPUS..................................................... fatigue, exhaustion
Kali Phosphoricum 6X HPUS ..................................................................tension
Kali Sulphuricum 6X HPUS................................................... fatigue, exhaustion
Magnesia Phosphorica 6X HPUS ............................. fatigue, exhaustion, tension
Natrum Muriaticum 6X HPUS ................................................................. fatigue
Natrum Phosphoricum 6X HPUS............................................................. fatigue
Natrum Sulphuricum 6X HPUS ............................................................... fatigue
Silicea 6X HPUS..................................................................................... fatigue

" HPUS" is the Homeopathic Pharmacopoeia of the United States

Uses

Temporarily relieves symptoms associated with

- General debility
- Fatigue
- Exhaustion
- Tension

Warnings

Ask a doctor before use if you have:

- Symptoms persist for more than 7 days or worsen
- New symptoms occur
- Redness, swelling, or inflammation is present
- Pain gets worse or lasts more than 7 days.

If pregnant or breastfeeding, ask a health professional before use. Keep out of reach of children.

Directions

- Use as directed
- Take 30 minutes away from food.

Adults:

- Acute dose: Chew 1 tablet every 30 minutes until symptoms subside, up to 6 times per day.
- Maintenance dose: Chew 1 tablet, 4 times daily.

Children 6 years and older:

- Acute dose: Crush ½ tablet, dissolve in water, and take every 30 minutes until symptoms subside, up to 6 times per day.
- Maintenance dose: Crush ½ tablet, dissolve in water, 4 times per day.

Other Information

Store below 86°F

Inactive Ingredients

Calcium hydrogen phosphate, Lactose, Magnesium stearate.

Questions? www.schuesslertissuesalts.co or + 1-888-464-6775